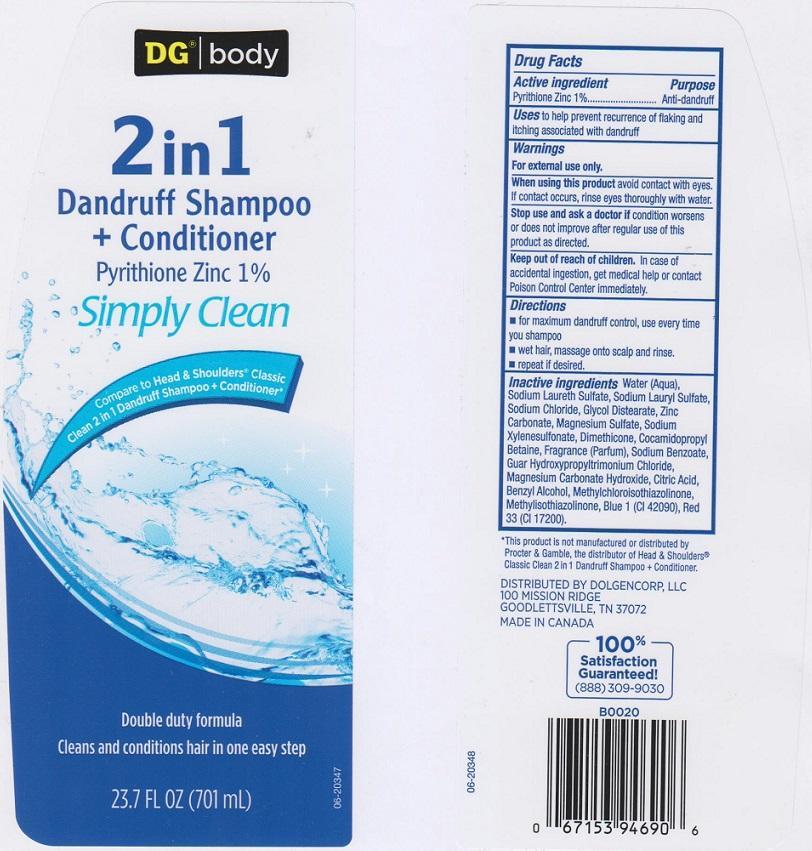 DRUG LABEL: DG BODY
NDC: 55910-426 | Form: LIQUID
Manufacturer: DOLGENCORP INC
Category: otc | Type: HUMAN OTC DRUG LABEL
Date: 20150528

ACTIVE INGREDIENTS: PYRITHIONE ZINC 10 mg/1 mL
INACTIVE INGREDIENTS: WATER; SODIUM LAURETH SULFATE; SODIUM LAURYL SULFATE; SODIUM CHLORIDE; GLYCOL DISTEARATE; ZINC CARBONATE; MAGNESIUM SULFATE; SODIUM XYLENESULFONATE; DIMETHICONE; COCAMIDOPROPYL BETAINE; SODIUM BENZOATE; GUAR HYDROXYPROPYLTRIMONIUM CHLORIDE (1.7 SUBSTITUENTS PER SACCHARIDE); MAGNESIUM CARBONATE HYDROXIDE; CITRIC ACID MONOHYDRATE; BENZYL ALCOHOL; METHYLCHLOROISOTHIAZOLINONE; METHYLISOTHIAZOLINONE; FD&C BLUE NO. 1; D&C RED NO. 33

DRUG FACTS

ACTIVE INGREDIENT

PYRITHIONE ZINC 1%

PURPOSE

ANTI-DANDRUFF

USES

TO HELP PREVENT RECURRENCE OF FLAKING AND ITCHING ASSOCIATED WITH DANDRUFF

WARNINGS

FOR EXTERNAL USE ONLY

WHEN USING THIS PRODUCT

AVOID CONTACT WITH EYES. IF CONTACT OCCURS, RINSE EYES THOROUGHLY WITH WATER

STOP USE AND ASK A DOCTOR IF

CONDITION WORSENS OR DOES NOT IMPROVE AFTER REGULAR USE OF THIS PRODUCT AS DIRECTED

KEEP OUT OF REACH OF CHILDREN

IN CASE OF ACCIDENTAL INGESTION, GET MEDICAL HELP OR CONTACT A POISON CONTROL CENTER IMMEDIATELY

DIRECTIONS

- FOR MAXIMUM DANDRUFF CONTROL, USE EVERY TIME YOU SHAMPOO
- WET HAIR, MASSAGE ONTO SCALP AND RINSE
- REPEAT IF DESIRED

INACTIVE INGREDIENTS

WATER (AQUA), SODIUM LAURETH SULFATE, SODIUM LAURYL SULFATE, SODIUM CHLORIDE, GLYCOL DISTEARATE, ZINC CARBONATE, MAGNESIUM SULFATE, SODIUM XYLENESULFONATE, DIMETHICONE, COCAMIDOPROPYL BETAINE, FRAGRANCE (PARFUM), SODIUM BENZOATE, GUAR HYDROXYPROPYLTRIMONIUM CHLORIDE, MAGNESIUM CARBONATE HYDROXIDE, CITRIC ACID, BENZYL ALCOHOL, METHYLCHLOROISOTHIAZOLINONE, METHYLISOTHIAZOLINONE, BLUE 1 (CI 42090), RED 33 (CI 17200).